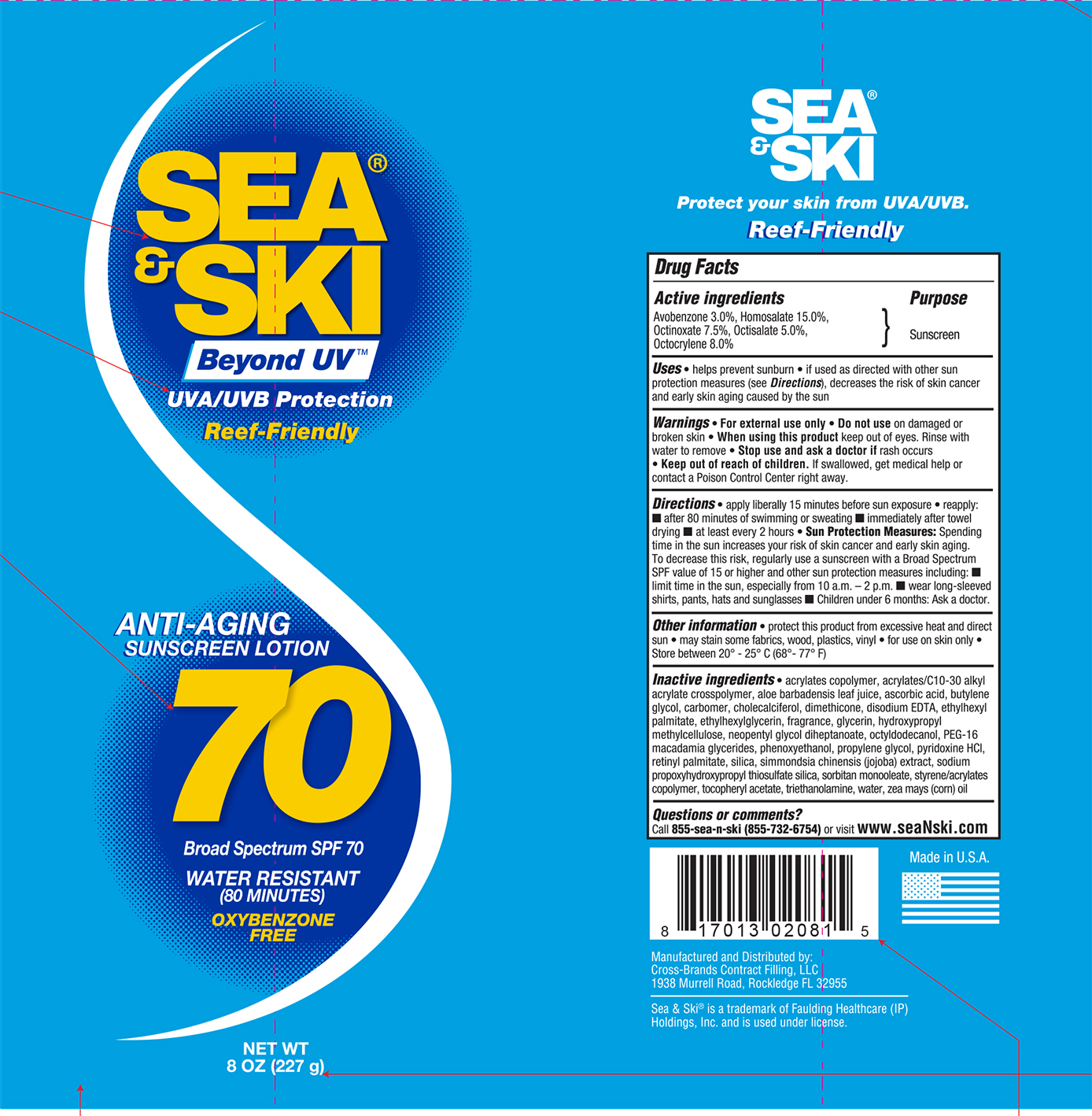 DRUG LABEL: Sea and Ski SPF 70
NDC: 73440-2081 | Form: LOTION
Manufacturer: Cross-Brands Contract FIlling
Category: otc | Type: HUMAN OTC DRUG LABEL
Date: 20210219

ACTIVE INGREDIENTS: AVOBENZONE 6.81 g/227 g; HOMOSALATE 34.05 g/227 g; OCTOCRYLENE 18.16 g/227 g; OCTISALATE 11.35 g/227 g; OCTINOXATE 17.03 g/227 g
INACTIVE INGREDIENTS: WATER 103.73 g/227 g

Sea&Ski SPF 70 8oz